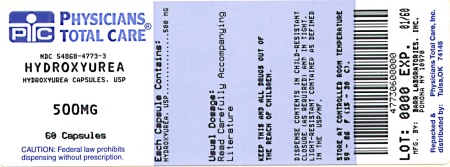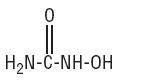 DRUG LABEL: HYDROXYUREA
NDC: 54868-4773 | Form: CAPSULE
Manufacturer: Physicians Total Care, Inc.
Category: prescription | Type: HUMAN PRESCRIPTION DRUG LABEL
Date: 20120601

ACTIVE INGREDIENTS: HYDROXYUREA 500 mg/1 1
INACTIVE INGREDIENTS: ANHYDROUS CITRIC ACID; BENZYL ALCOHOL; FERROSOFERRIC OXIDE; BUTYLPARABEN; CARBOXYMETHYLCELLULOSE SODIUM; D&C RED NO. 28; D&C YELLOW NO. 10; ALUMINUM OXIDE; SODIUM PHOSPHATE, DIBASIC; EDETATE CALCIUM DISODIUM; FD&C BLUE NO. 1; FD&C BLUE NO. 2; FD&C RED NO. 40; GELATIN; LACTOSE MONOHYDRATE; MAGNESIUM STEARATE; METHYLPARABEN; SHELLAC; PROPYLPARABEN SODIUM; PROPYLENE GLYCOL; FERRIC OXIDE RED; SODIUM LAURYL SULFATE; SODIUM PROPIONATE; TITANIUM DIOXIDE

HYDROXYUREA CAPSULES USP

Rx only

DESCRIPTION

Hydroxyurea capsules USP are an antineoplastic agent available for oral use as capsules providing 500 mg hydroxyurea, USP. Inactive ingredients: anhydrous citric acid, benzyl alcohol, black iron oxide, butylparaben, carboxymethylcellulose sodium, D & C red no. 28, D & C yellow no. 10 aluminum lake, dibasic sodium phosphate, edetate calcium disodium, FD & C blue no. 1, FD & C blue no. 1 aluminum lake, FD & C blue no. 2 aluminum lake, FD & C red no. 40, FD & C red no. 40 aluminum lake, gelatin, lactose monohydrate, magnesium stearate, methylparaben, pharmaceutical glaze, propylparaben, propylene glycol, red iron oxide, sodium lauryl sulfate, sodium propionate, and titanium dioxide.

Hydroxyurea is an essentially tasteless, white crystalline powder. Its structural formula is:

CH4N2O2 M.W. 76.05

CLINICAL PHARMACOLOGY

Mechanism of Action

The precise mechanism by which hydroxyurea produces its antineoplastic effects cannot, at present, be described. However, the reports of various studies in tissue culture in rats and humans lend support to the hypothesis that hydroxyurea causes an immediate inhibition of DNA synthesis by acting as a ribonucleotide reductase inhibitor, without interfering with the synthesis of ribonucleic acid or of protein. This hypothesis explains why, under certain conditions, hydroxyurea may induce teratogenic effects.

Three mechanisms of action have been postulated for the increased effectiveness of concomitant use of hydroxyurea therapy with irradiation on squamous cell (epidermoid) carcinomas of the head and neck. In vitro studies utilizing Chinese hamster cells suggest that hydroxyurea (1) is lethal to normally radioresistant S-stage cells, and (2) holds other cells of the cell cycle in the G1 or pre-DNA synthesis stage where they are most susceptible to the effects of irradiation. The third mechanism of action has been theorized on the basis of in vitro studies of HeLa cells: it appears that hydroxyurea, by inhibition of DNA synthesis, hinders the normal repair process of cells damaged but not killed by irradiation, thereby decreasing their survival rate; RNA and protein syntheses have shown no alteration.

Pharmacokinetics

Absorption

Hydroxyurea is readily absorbed after oral administration. Peak plasma levels are reached in 1 to 4 hours after an oral dose. With increasing doses, disproportionately greater mean peak plasma concentrations and AUCs are observed.

There are no data on the effect of food on the absorption of hydroxyurea.

Distribution

Hydroxyurea distributes rapidly and widely in the body with an estimated volume of distribution approximating total body water.

Plasma to ascites fluid ratios range from 2:1 to 7.5:1. Hydroxyurea concentrates in leukocytes and erythrocytes.

Metabolism

Up to 60% of an oral dose undergoes conversion through metabolic pathways that are not fully characterized. One pathway is probably saturable hepatic metabolism. Another minor pathway may be degradation by urease found in intestinal bacteria. Acetohydroxamic acid was found in the serum of three leukemic patients receiving hydroxyurea and may be formed from hydroxylamine resulting from action of urease on hydroxyurea.

Excretion

Excretion of hydroxyurea in humans is likely a linear first-order renal process.

Special Populations

Geriatric, Gender, Race

No information is available regarding pharmacokinetic differences due to age, gender, or race.

Pediatric

No pharmacokinetic data are available in pediatric patients treated with hydroxyurea.

Renal Insufficiency

As renal excretion is a pathway of elimination, consideration should be given to decreasing the dosage of hydroxyurea in patients with renal impairment. In adult patients with sickle cell disease, an open-label, non-randomized, single-dose, multicenter study was conducted to assess the influence of renal function on the pharmacokinetics of hydroxyurea. Patients in the study with normal renal function (creatinine clearance [CrCl] > 80 mL/min), mild (CrCl 50 to 80 mL/min), moderate (CrCl = 30 to < 50 mL/min), or severe (< 30 mL/min) renal impairment received hydroxyurea as a single oral dose of 15 mg/kg, achieved by using combinations of the 200 mg, 300 mg, or 400 mg capsules. Patients with end-stage renal disease (ESRD) received two doses of 15 mg/kg separated by 7 days, the first was given following a 4 hour hemodialysis session, the second prior to hemodialysis. In this study, the mean exposure (AUC) in patients whose creatinine clearance was < 60 mL/min (or ESRD) was approximately 64% higher than in patients with normal renal function. The results suggest that the initial dose of hydroxyurea should be reduced when used to treat patients with renal impairment (see PRECAUTIONS and DOSAGE ANDADMINISTRATION). Close monitoring of hematologic parameters is advised in these patients.

Hepatic Insufficiency

There are no data that support specific guidance for dosage adjustment in patients with hepatic impairment. Close monitoring of hematologic parameters is advised in these patients.

Drug Interactions

There are no data on concomitant use of hydroxyurea with other drugs in humans.

Animal Pharmacology and Toxicology

The oral LD50 of hydroxyurea is 7330 mg/kg in mice and 5780 mg/kg in rats, given as a single dose.

In subacute and chronic toxicity studies in the rat, the most consistent pathological findings were an apparent dose-related mild to moderate bone marrow hypoplasia as well as pulmonary congestion and mottling of the lungs. At the highest dosage levels (1260 mg/kg/day for 37 days, then 2520 mg/kg/day for 40 days), testicular atrophy with absence of spermatogenesis occurred; in several animals, hepatic cell damage with fatty metamorphosis was noted. In the dog, mild to marked bone marrow depression was a consistent finding except at the lower dosage levels. Additionally, at the higher dose levels (140 to 420 mg or 140 to 1260 mg/kg/week given 3 or 7 days weekly for 12 weeks), growth retardation, slightly increased blood glucose values, and hemosiderosis of the liver or spleen were found; reversible spermatogenic arrest was noted. In the monkey, bone marrow depression, lymphoid atrophy of the spleen, and degenerative changes in the epithelium of the small and large intestines were found. At the higher, often lethal, doses (400 to 800 mg/kg/day for 7 to 15 days), hemorrhage and congestion were found in the lungs, brain, and urinary tract. Cardiovascular effects (changes in heart rate, blood pressure, orthostatic hypotension, EKG changes) and hematological changes (slight hemolysis, slight methemoglobinemia) were observed in some species of laboratory animals at doses exceeding clinical levels.

INDICATIONS AND USAGE

Significant tumor response to hydroxyurea capsules USP has been demonstrated in melanoma, resistant chronic myelocytic leukemia, and recurrent, metastatic, or inoperable carcinoma of the ovary.

Hydroxyurea, USP used concomitantly with irradiation therapy is intended for use in the local control of primary squamous cell (epidermoid) carcinomas of the head and neck, excluding the lip.

CONTRAINDICATIONS

Hydroxyurea is contraindicated in patients with marked bone marrow depression, i.e., leukopenia (< 2500 WBC) or thrombocytopenia (< 100,000), or severe anemia.

Hydroxyurea capsules are contraindicated in patients who have demonstrated a previous hypersensitivity to hydroxyurea or any other component of its formulation.

WARNINGS

Treatment with hydroxyurea should not be initiated if bone marrow function is markedly depressed (see CONTRAINDICATIONS). Bone marrow suppression may occur, and leukopenia is generally its first and most common manifestation. Thrombocytopenia and anemia occur less often and are seldom seen without a preceding leukopenia. However, the recovery from myelosuppression is rapid when therapy is interrupted. It should be borne in mind that bone marrow depression is more likely in patients who have previously received radiotherapy or cytotoxic cancer chemotherapeutic agents; hydroxyurea should be used cautiously in such patients.

Patients who have received irradiation therapy in the past may have an exacerbation of postirradiation erythema.

In HIV-infected patients during therapy with hydroxyurea and didanosine, with or without stavudine, fatal and nonfatal pancreatitis have occurred. Hepatotoxicity and hepatic failure resulting in death have been reported during postmarketing surveillance in HIV-infected patients treated with hydroxyurea and other antiretroviral agents. Fatal hepatic events were reported most often in patients treated with the combination of hydroxyurea, didanosine, and stavudine. This combination should be avoided.

Peripheral neuropathy, which was severe in some cases, has been reported in HIV-infected patients receiving hydroxyurea in combination with antiretroviral agents, including didanosine, with or without stavudine.

Severe anemia must be corrected before initiating therapy with hydroxyurea.

Erythrocytic abnormalities: megaloblastic erythropoiesis, which is self-limiting, is often seen early in the course of hydroxyurea therapy. The morphologic change resembles pernicious anemia, but is not related to vitamin B12 or folic acid deficiency. Hydroxyurea may also delay plasma iron clearance and reduce the rate of iron utilization by erythrocytes, but it does not appear to alter the red blood cell survival time.

Elderly patients may be more sensitive to the effects of hydroxyurea, and may require a lower dose regimen (see PRECAUTIONS, Geriatric Use).

In patients receiving long-term hydroxyurea for myeloproliferative disorders, such as polycythemia vera and thrombocythemia, secondary leukemia has been reported. It is unknown whether this leukemogenic effect is secondary to hydroxyurea or associated with the patient’s underlying disease.

Cutaneous vasculitic toxicities, including vasculitic ulcerations and gangrene, have occurred in patients with myeloproliferative disorders during therapy with hydroxyurea. These vasculitic toxicities were reported most often in patients with a history of, or currently receiving, interferon therapy. Due to potentially severe clinical outcomes for the cutaneous vasculitic ulcers reported in patients with myeloproliferative disease, hydroxyurea should be discontinued if cutaneous vasculitic ulcerations develop and alternative cytoreductive agents should be initiated as indicated.

Carcinogenesis and Mutagenesis

Hydroxyurea is genotoxic in a wide range of test systems and is thus presumed to be a human carcinogen. In patients receiving long-term hydroxyurea for myeloproliferative disorders, such as polycythemia vera and thrombocythemia, secondary leukemia has been reported. It is unknown whether this leukemogenic effect is secondary to hydroxyurea or is associated with the patient’s underlying disease. Skin cancer has also been reported in patients receiving long-term hydroxyurea.

Conventional long-term studies to evaluate the carcinogenic potential of hydroxyurea have not been performed. However, intraperitoneal administration of 125 to 250 mg/kg hydroxyurea (about 0.6 to 1.2 times the maximum recommended human oral daily dose on a mg/m^2 basis) thrice weekly for 6 months to female rats increased the incidence of mammary tumors in rats surviving to 18 months compared to control. Hydroxyurea is mutagenic in vitro to bacteria, fungi, protozoa, and mammalian cells. Hydroxyurea is clastogenic in vitro (hamster cells, human lymphoblasts) and in vivo (SCE assay in rodents, mouse micronucleus assay). Hydroxyurea causes the transformation of rodent embryo cells to a tumorigenic phenotype.

Pregnancy

Drugs which affect DNA synthesis, such as hydroxyurea, may be potential mutagenic agents. The physician should carefully consider this possibility before administering this drug to male or female patients who may contemplate conception.

Hydroxyurea capsules can cause fetal harm when administered to a pregnant woman. Hydroxyurea has been demonstrated to be a potent teratogen in a wide variety of animal models, including mice, hamsters, cats, miniature swine, dogs, and monkeys at doses within 1 fold of the human dose given on a mg/m^2 basis. Hydroxyurea is embryotoxic and causes fetal malformations (partially ossified cranial bones, absence of eye sockets, hydrocephaly, bipartite sternebrae, missing lumbar vertebrae) at 180 mg/kg/day (about 0.8 times the maximum recommended human daily dose on a mg/m^2 basis) in rats and at 30 mg/kg/day (about 0.3 times the maximum recommended human daily dose on a mg/m^2 basis) in rabbits. Embryotoxicity was characterized by decreased fetal viability, reduced live litter sizes, and developmental delays. Hydroxyurea crosses the placenta. Single doses of ≥ 375 mg/kg (about 1.7 times the maximum recommended human daily dose on a mg/m^2 basis) to rats caused growth retardation and impaired learning ability. There are no adequate and well-controlled studies in pregnant women. If this drug is used during pregnancy or if the patient becomes pregnant while taking this drug, the patient should be apprised of the potential harm to the fetus. Women of childbearing potential should be advised to avoid becoming pregnant.

PRECAUTIONS

General

Therapy with hydroxyurea requires close supervision. The complete status of the blood, including bone marrow examination, if indicated, as well as kidney function and liver function should be determined prior to, and repeatedly during, treatment. The determination of the hemoglobin level, total leukocyte counts, and platelet counts should be performed at least once a week throughout the course of hydroxyurea therapy. If the white blood cell count decreases to less than 2500/mm^3, or the platelet count to less than 100,000/mm^3, therapy should be interrupted until the values rise significantly toward normal levels. Severe anemia, if it occurs, should be managed without interrupting hydroxyurea therapy.

Hydroxyurea should be used with caution in patients with marked renal dysfunction (see CLINICAL PHARMACOLOGY, Special Populations and DOSAGE AND ADMINISTRATION).

Hydroxyurea is not indicated for the treatment of HIV infection; however, if HIV-infected patients are treated with hydroxyurea, and in particular, in combination with didanosine and/or stavudine, close monitoring for signs and symptoms of pancreatitis is recommended. Patients who develop signs and symptoms of pancreatitis should permanently discontinue therapy with hydroxyurea (see WARNINGS and ADVERSE REACTIONS).

An increased risk of hepatotoxicity, which may be fatal, may occur in patients treated with hydroxyurea, and in particular, in combination with didanosine and stavudine. This combination should be avoided.

Carcinogenesis, Mutagenesis, Impairment of Fertility

See WARNINGS for Carcinogenesis and Mutagenesis information.

Impairment of Fertility

Hydroxyurea administered to male rats at 60 mg/kg/day (about 0.3 times the maximum recommended human daily dose on a mg/m^2 basis) produced testicular atrophy, decreased spermatogenesis, and significantly reduced their ability to impregnate females.

Pregnancy

Teratogenic Effects

Pregnancy Category D

(See WARNINGS.)

Nursing Mothers

Hydroxyurea is excreted in human milk.

Because of the potential for serious adverse reactions with hydroxyurea, a decision should be made whether to discontinue nursing or to discontinue the drug, taking into account the importance of the drug to the mother.

Pediatric Use

Safety and effectiveness in pediatric patients have not been established.

Geriatric Use

Elderly patients may be more sensitive to the effects of hydroxyurea, and may require a lower dose regimen.

This drug is known to be excreted by the kidney, and the risk of toxic reactions to this drug may be greater in patients with impaired renal function. Because elderly patients are more likely to have decreased renal function, care should be taken in dose selection, and it may be useful to monitor renal function (see DOSAGE AND ADMINISTRATION, Renal Insufficiency).

Drug Interactions

Prospective studies on the potential for hydroxyurea to interact with other drugs have not been performed.

Concurrent use of hydroxyurea and other myelosuppressive agents or radiation therapy may increase the likelihood of bone marrow depression or other adverse events (see WARNINGS and ADVERSE REACTIONS).

Studies have shown that there is an analytical interference of hydroxyurea with the enzymes (urease, uricase, and lactate dehydrogenase) used in the determination of urea, uric acid and lactic acid, rendering falsely elevated results of these in patients treated with hydroxyurea.

Information for Patients

Hydroxyurea capsules are a medication that must be handled with care. People who are not taking hydroxyurea capsules should not be exposed to it. To decrease the risk of exposure, wear disposable gloves when handling hydroxyurea capsules or bottles containing hydroxyurea capsules. Anyone handling hydroxyurea capsules should wash their hands before and after contact with the bottle or capsules. If the powder from the capsule is spilled, it should be wiped up immediately with a damp disposable towel and discarded in a closed container, such as a plastic bag. The medication should be kept away from children and pets. Contact your doctor for instructions on how to dispose of outdated capsules.

ADVERSE REACTIONS

Reported adverse reactions are bone marrow depression (leukopenia, anemia, and thrombocytopenia), gastrointestinal symptoms (stomatitis, anorexia, nausea, vomiting, diarrhea, and constipation), and dermatological reactions such as maculopapular rash, skin ulceration, dermatomyositis-like skin changes, peripheral and facial erythema. Hyperpigmentation, atrophy of skin and nails, scaling, and violet papules have been observed in some patients after several years of long-term daily maintenance therapy with hydroxyurea capsules. Skin cancer has been reported. Cutaneous vasculitic toxicities, including vasculitic ulcerations and gangrene, have occurred in patients with myeloproliferative disorders during therapy with hydroxyurea. These vasculitic toxicities were reported most often in patients with a history of, or currently receiving, interferon therapy (see WARNINGS). Dysuria and alopecia have been reported. Large doses may produce moderate drowsiness. Neurological disturbances have occurred and were limited to headache, dizziness, disorientation, hallucinations, and convulsions. Hydroxyurea capsules may cause temporary impairment of renal tubular function accompanied by elevations in serum uric acid, blood urea nitrogen (BUN), and creatinine levels. Abnormal bromsulphalein (BSP) retention has been reported. Fever, chills, malaise, edema, asthenia, and elevation of hepatic enzymes have also been reported.

Adverse reactions observed with combined hydroxyurea and irradiation therapy are similar to those reported with the use of hydroxyurea or radiation treatment alone. These effects primarily include bone marrow depression (anemia and leukopenia), gastric irritation, and mucositis. Almost all patients receiving an adequate course of combined hydroxyurea and irradiation therapy will demonstrate concurrent leukopenia. Platelet depression (< 100,000 cells/mm^3) has occurred in the presence of marked leukopenia. Hydroxyurea capsules may potentiate some adverse reactions usually seen with irradiation alone, such as gastric distress and mucositis.

The association of hydroxyurea with the development of acute pulmonary reactions consisting of diffuse pulmonary infiltrates, fever, and dyspnea has been reported. Pulmonary fibrosis also has been reported.

In HIV-infected patients who received hydroxyurea in combination with antiretroviral agents, in particular, didanosine plus stavudine, fatal and nonfatal pancreatitis and hepatotoxicity, and severe peripheral neuropathy have been reported. Patients treated with hydroxyurea in combination with didanosine, stavudine, and indinavir in Study ACTG 5025 showed a median decline in CD4 cells of approximately 100/mm^3 (see WARNINGS and PRECAUTIONS).

OVERDOSAGE

Acute mucocutaneous toxicity has been reported in patients receiving hydroxyurea at dosages several times the therapeutic dose. Soreness, violet erythema, edema on palms and soles followed by scaling of hands and feet, severe generalized hyperpigmentation of the skin, and stomatitis have also been observed.

DOSAGE AND ADMINISTRATION

Procedures for proper handling and disposal of cytotoxic drugs should be considered. Several guidelines on this subject have been published.^1-4

To minimize the risk of dermal exposure, always wear impervious gloves when handling bottles containing hydroxyurea capsules. Hydroxyurea capsules should not be opened. Personnel should avoid exposure to crushed or opened capsules. If contact with crushed or opened capsules occurs, wash immediately and thoroughly. More information is available in the references listed below.

Because of the rarity of melanoma, resistant chronic myelocytic leukemia, carcinoma of the ovary, and carcinomas of the head and neck in pediatric patients, dosage regimens have not been established.

All dosage should be based on the patient’s actual or ideal weight, whichever is less. Concurrent use of hydroxyurea capsules with other myelosuppressive agents may require adjustment of dosages.

Since hydroxyurea may raise the serum uric acid level, dosage adjustment of uricosuric medication may be necessary.

Solid Tumors

Intermittent Therapy

80 mg/kg administered orally as a single dose every third day

Continuous Therapy

20 to 30 mg/kg administered orally as a single dose daily

Concomitant Therapy with Irradiation

Carcinoma of the head and neck

80 mg/kg administered orally as a single dose every third day

Administration of hydroxyurea should begin at least seven days before initiation of irradiation and continued during radiotherapy as well as indefinitely afterwards provided that the patient may be kept under adequate observation and evidences no unusual or severe reactions.

Resistant Chronic Myelocytic Leukemia

Until the intermittent therapy regimen has been evaluated, CONTINUOUS therapy (20 to 30 mg/kg administered orally as a single dose daily) is recommended.

An adequate trial period for determining the antineoplastic effectiveness of hydroxyurea is six weeks of therapy. When there is regression in tumor size or arrest in tumor growth, therapy should be continued indefinitely. Therapy should be interrupted if the white blood cell count drops below 2500/mm^3, or the platelet count below 100,000/mm^3. In these cases, the counts should be reevaluated after three days, and therapy resumed when the counts return to acceptable levels. Since the hematopoietic rebound is prompt, it is usually necessary to omit only a few doses. If prompt rebound has not occurred during combined hydroxyurea capsules and irradiation therapy, irradiation may also be interrupted. However, the need for postponement of irradiation has been rare; radiotherapy has usually been continued using the recommended dosage and technique. Severe anemia, if it occurs, should be corrected without interrupting hydroxyurea therapy. Because hematopoiesis may be compromised by extensive irradiation or by other antineoplastic agents, it is recommended that hydroxyurea be administered cautiously to patients who have recently received extensive radiation therapy or chemotherapy with other cytotoxic drugs.

Pain or discomfort from inflammation of the mucous membranes at the irradiated site (mucositis) is usually controlled by measures such as topical anesthetics and orally administered analgesics. If the reaction is severe, hydroxyurea therapy may be temporarily interrupted; if it is extremely severe, irradiation dosage may, in addition, be temporarily postponed. However, it has rarely been necessary to terminate these therapies.

Severe gastric distress, such as nausea, vomiting, and anorexia, resulting from combined therapy may usually be controlled by temporary interruption of hydroxyurea administration.

Renal Insufficiency

As renal excretion is a pathway of elimination, consideration should be given to decreasing the dosage of hydroxyurea capsules in patients with renal impairment (see PRECAUTIONS and CLINICAL PHARMACOLOGY). Close monitoring of hematologic parameters is advised in these patients.

Hepatic Insufficiency

There are no data that support specific guidance for dosage adjustment in patients with hepatic impairment. Close monitoring of hematologic parameters is advised in these patients.

HOW SUPPLIED

Hydroxyurea capsules USP 500 mg are available as a two-piece hard gelatin capsule with purple opaque cap and pink opaque body filled with white powder, imprinted in black ink barr 882 and packaged in

Bottles of 30 | NDC 54868-4773-0
Bottles of 40 | NDC 54868-4773-4
Bottles of 50 | NDC 54868-4773-2
Bottles of 60 | NDC 54868-4773-3
Bottles of 100 | NDC 54868-4773-1

Store at 20º to 25ºC (68º to 77ºF) [See USP Controlled Room Temperature].

Dispense in a tight, light-resistant container as defined in the USP, with a child-resistant closure (as required).

STORE IN A DRY ATMOSPHERE AND AVOID EXCESSIVE HEAT.

WEAR GLOVES AT ALL TIMES WHEN HANDLING CONTAINERS.

KEEP THIS AND ALL MEDICATIONS OUT OF THE REACH OF CHILDREN.

REFERENCES

1. NIOSH Alert: Preventing occupational exposures to antineoplastic and other hazardous drugs in healthcare settings. 2004. U.S. Department of Health and Human Services, Public Health Service, Centers for Disease Control and Prevention, National Institute for Occupational Safety and Health, DHHS (NIOSH) Publication No. 2004-165.
2. OSHA Technical Manual, TED 1-0.15A, Section VI: Chapter 2. Controlling Occupational Exposure to Hazardous Drugs. OSHA, 1999. http://www.osha.gov/dts/osta/otm/otm_vi/otm_vi_2.html
3. American Society of Health-System Pharmacists. ASHP guidelines on handling hazardous drugs. Am J Health-Syst Pharm. 2006;63:1172-1193.
4. Polovich M, White JM, Kelleher LO, eds. 2005. Chemotherapy and biotherapy guidelines and recommendations for practice. 2nd ed. Pittsburgh, PA: Oncology Nursing Society.

TEVA PHARMACEUTICALS USA
Sellersville, PA 18960

Rev. A 2/2012

Relabeling and Repackaging by:
Physicians Total Care, Inc.
Tulsa, Oklahoma 74146

PRINCIPAL DISPLAY PANEL

Hydroxyurea Capsules USP 500 mg Label Text

HYDROXYUREA
Capsules USP
500 mg

Caution: Cytotoxic, Special
Handling Procedures

Rx only